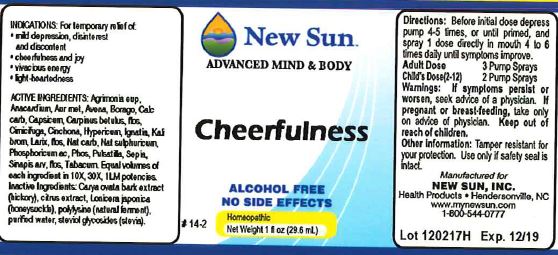 DRUG LABEL: Cheerfulness
NDC: 66579-0082 | Form: LIQUID
Manufacturer: New Sun Inc.
Category: homeopathic | Type: HUMAN OTC DRUG LABEL
Date: 20180215

ACTIVE INGREDIENTS: AGRIMONIA EUPATORIA 10 [hp_X]/29 mL; SEMECARPUS ANACARDIUM JUICE 10 [hp_X]/29 mL; GOLD 10 [hp_X]/29 mL; AVENA SATIVA FLOWERING TOP 10 [hp_X]/29 mL; BORAGE 10 [hp_X]/29 mL; OYSTER SHELL CALCIUM CARBONATE, CRUDE 10 [hp_X]/29 mL; CAPSICUM 10 [hp_X]/29 mL; CARPINUS BETULUS FLOWERING TOP 10 [hp_X]/29 mL; BLACK COHOSH 10 [hp_X]/29 mL; CINCHONA OFFICINALIS BARK 10 [hp_X]/29 mL; HYPERICUM PERFORATUM 10 [hp_X]/29 mL; STRYCHNOS IGNATII SEED 10 [hp_X]/29 mL; POTASSIUM BROMIDE 10 [hp_X]/29 mL; LARIX DECIDUA FLOWERING TOP 10 [hp_X]/29 mL; SODIUM CARBONATE 10 [hp_X]/29 mL; SODIUM SULFATE 10 [hp_X]/29 mL; PHOSPHORIC ACID 10 [hp_X]/29 mL; PHOSPHORUS 10 [hp_X]/29 mL; PULSATILLA VULGARIS 10 [hp_X]/29 mL; SEPIA OFFICINALIS JUICE 10 [hp_X]/29 mL; SINAPIS ARVENSIS FLOWERING/FRUITING TOP 10 [hp_X]/29 mL; TOBACCO LEAF 10 [hp_X]/29 mL
INACTIVE INGREDIENTS: CARYA OVATA BARK; CITRUS BIOFLAVONOIDS; LONICERA JAPONICA FLOWER; POLYEPSILON-LYSINE (4000 MW); WATER; REBAUDIOSIDE A

Cheerfulness

DOSAGE AND ADMINISTRATION

Directions: Before initial dose depress pump 4-5 times or until primed and spray 1 dose directly in mouth 4 to 6 times daily until symptoms improve.

Adult Dose: 3 Pump Sprays

Child's Dose (2-12): 2 Pump Sprays

WARNINGS

Warnings: If symptoms persist or worsen, seek advice of a physician. If pregnant or breast-feeding, take only on advice of physician.

Keep out of reach of children.

Other information: Tamper resistant for your protection. Use only if safety seal is intact.

PURPOSE

Indications: For temporary relief of: •mild depression, disinterest and discontent •cheerfulness and joy •vivacious energy •light heartedness

ACTIVE INGREDIENT

Active Ingredients: Agrimonia eup, Anacardium, Aur met, Avena, Borago, Calc carb, Capsicum, Carpinus betulus, flos, Cimicifuga, Cinchona, Hypericum, Ignatia, Kali brom, Larix, flos, Nat carb, Nat sulphuricum, Phosphoricum ac, Phos, Pulsatilla, Sepia, Sinapis arv, flos, Tabacum.

Equal volumes of each ingredient in 10X, 30X, and 1LM potencies.

Inactive Ingredient: Carya ovata bark extract (hickory), citrus extract, Lonicera japonica (honeysuckle) polylysine (natural ferment), purified water, steviol glycosides (stevia)

Indications

For temporary relief of:

- mild depression, disinterest and discontent
- cheerfulness and joy
- vivacious energy
- light-heartedness